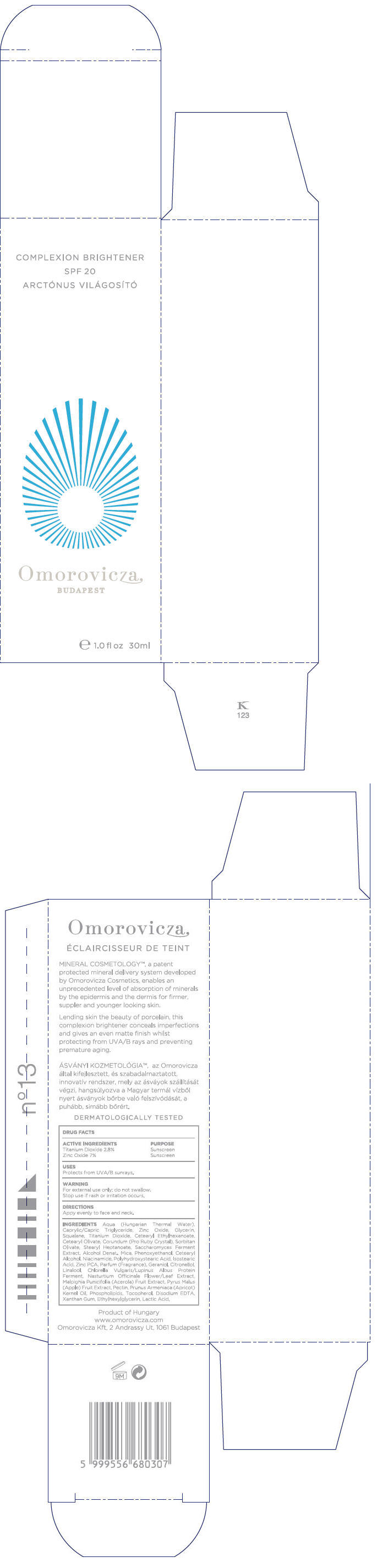 DRUG LABEL: Complexion Brightener SPF20
NDC: 41442-123 | Form: CREAM
Manufacturer: Omorovicza Kozmetikai Kft.
Category: otc | Type: HUMAN OTC DRUG LABEL
Date: 20110301

ACTIVE INGREDIENTS: Titanium dioxide 0.84 mL/30 mL; Zinc oxide 2.1 mL/30 mL
INACTIVE INGREDIENTS: Caprylic/Capric Mono/Diglycerides; Glycerin; Squalane; Cetearyl Ethylhexanoate; Cetearyl Olivate; Sorbitan Olivate; Stearyl Heptanoate; Alcohol; Mica; Phenoxyethanol; Cetostearyl Alcohol; Niacinamide; Polyhydroxystearic Acid (2300 MW); Isostearic Acid; Zinc Pidolate; Geraniol; .BETA.-CITRONELLOL, (+/-)-; LINALOOL, (+)-; Rorippa Nasturtium-Aquaticum Flowering Top; Acerola; Apple; Pectin; Apricot Seed Oil; Alpha-Tocopherol; Edetate Disodium; Xanthan Gum; Ethylhexylglycerin; Lactic Acid

Complexion Brightener SPF20

DRUG FACTS

ACTIVE INGREDIENT

ACTIVE INGREDIENTS | PURPOSE
Titanium Dioxide 2.8% | Sunscreen
Zinc Oxide 7% | Sunscreen

USES

Protects from UVA/B sunrays

WARNING

For external use only; do not swallow.

Stop use if rash or irritation occurs.

DIRECTIONS

Apply evenly to face and neck.

INGREDIENTS

Aqua (Hungarian Thermal Water), Caprylic/Capric Triglyceride, Zinc Oxide, Glycerin, Squalane, Titanium Dioxide, Cetearyl Ethylhexanoate, Cetearyl Olivate, Corundum (Pro Ruby Crystal), Sorbitan Olivate, Stearyl Heptanoate, Saccharomyces Ferment Extract, Alcohol Denat., Mica, Phenoxyethanol, Cetearyl Alcohol, Niacinamide, Polyhydroxystearic Acid, Isostearic Acid, Zinc PCA, Parfum (Fragrance), Geraniol, Citronellol, Linalool, Chlorella Vulgaris/Lupinus Albus Protein Ferment, Nasturtium Officinale Flower/Leaf Extract, Malpighia Punicifolia (Acerola) Fruit Extract, Pyrus Malus (Apple) Fruit Extract, Pectin, Prunus Armeniaca (Apricot) Kernel Oil, Phospholipids, Tocopherol, Disodium EDTA, Xanthan Gum, Ethylhexylglycerin, Lactic Acid

PRINCIPAL DISPLAY PANEL - 30ml Bottle Carton

COMPLEXION BRIGHTENER
SPF 20
ARCTÓNUS VILÁGOSÍTÓ

Omorovicza
BUDAPEST

e 1.0 fl oz 30ml